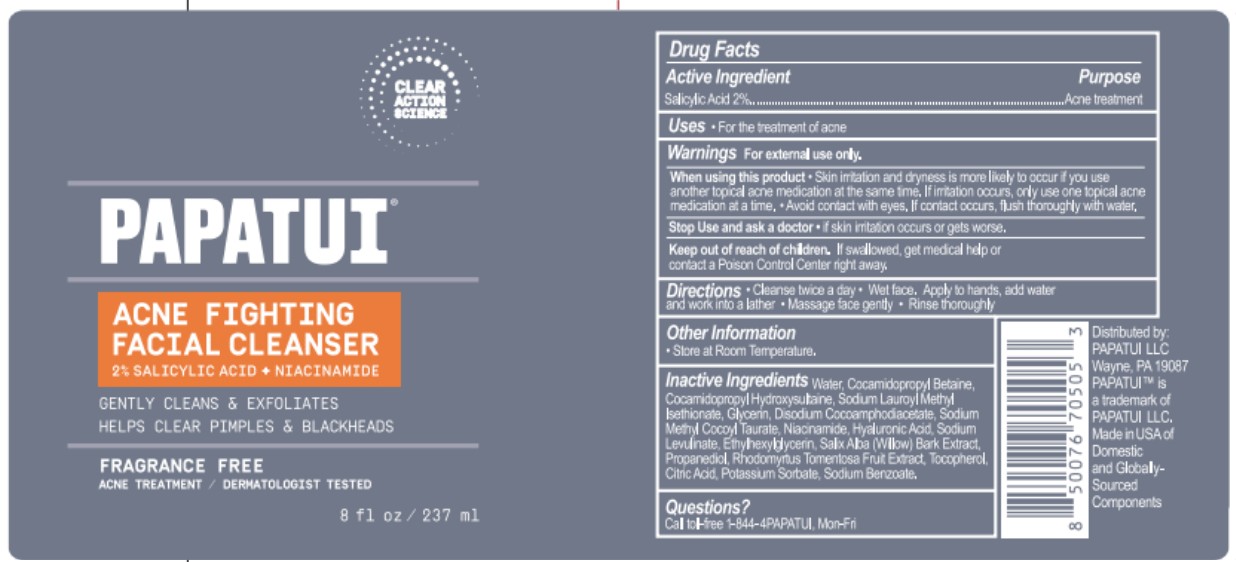 DRUG LABEL: PAPATUI Acne Fighting Facial Cleanser
NDC: 83850-210 | Form: LIQUID
Manufacturer: PAPATUI, LLC
Category: otc | Type: HUMAN OTC DRUG LABEL
Date: 20250822

ACTIVE INGREDIENTS: SALICYLIC ACID 2 g/100 mL
INACTIVE INGREDIENTS: POTASSIUM SORBATE; SODIUM LAUROYL METHYL ISETHIONATE; HYALURONIC ACID; SODIUM METHYL COCOYL TAURATE; SODIUM BENZOATE; GLYCERIN; DISODIUM COCOAMPHODIACETATE; WATER; SODIUM LEVULINATE; ETHYLHEXYLGLYCERIN; RHODOMYRTUS TOMENTOSA FRUIT; CITRIC ACID; SALIX ALBA BARK; COCAMIDOPROPYL HYDROXYSULTAINE; NIACINAMIDE; PROPANEDIOL; TOCOPHEROL; COCAMIDOPROPYL BETAINE

PAPATUI Acne Fighting Facial Cleanser

Drug Facts

Active Ingredient

Active Ingredient | Purpose
Salicylic Acid 2% | Acne Treatment

Uses

- For the treatment of acne

Warnings

For external use only

When using this product

- Skin irritation and dryness is more likely to occur if you use another topical acne medication at the same time. Iff irritation occurs, only use one topical acne medication at a time.
- Avoid contact with eyes. If contact occurs, flush thoroughly with water.

Stop use and ask a doctor

- If skin irritation occurs or gets worse.

Keep out of reach of children. If swallowed, get medical help or contact a Poison Control Center right away.

Directions

- Cleanse twice a day
- Wet face. Apply to hands, add water and work into a lather
- Massage face gently
- Rinse thoroughly

Other Information

- Store at Room Temperature

Inactive Ingredients

Water, Cocamidopropyl Betaine, Cocamidopropyl Hydroxysultaine, Sodium Lauroyl Methyl Isethionate, Glycerin, Disodium Cocoamphodiacetate, Sodium Methyl Cocoyl Taurate, Niacinamide, Hyaluronic Acid, Sodium Levulinate, Ethylhexylglycerin, Salix Alba (Willow) Bark Extract, Propanediol, Rhodomyrtus Tomentosa Fruit Extract, Tocopherol, Citric Acid, Potassium Sorbate, Sodium Benzoate.

Questions?

Call toll-free 1-844-4PAPATUI Mon-Fri

PRINCIPAL DISPLAY PANEL - 237 mL Bottle

PAPATUI

CLEAR ACTION SCIENCE

ACNE FIGHTING

FACIAL CLEANSER

2% SALICYLIC ACID + NIACINAMIDE

GENTLY CLEANS & EXFOLIATES

HELPS CLEAR PIMPLES & BLACKHEADS

FRAGRANCE FREE

ACNE TREATMENT / DERMATOLOGIST TESTED

8 fl oz / 237 ml